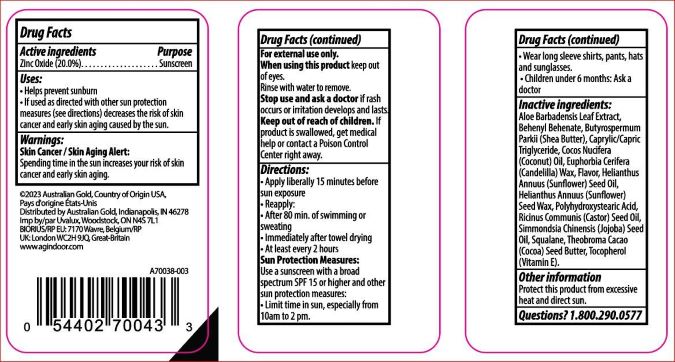 DRUG LABEL: SPF 50 Sunscreen Stick
NDC: 84061-129 | Form: STICK
Manufacturer: Australian Gold
Category: otc | Type: HUMAN OTC DRUG LABEL
Date: 20260123

ACTIVE INGREDIENTS: ZINC OXIDE 200 mg/1 g
INACTIVE INGREDIENTS: COCONUT OIL 395 mg/1 g; WHITE WAX 162 mg/1 g; COCOA BUTTER 57 mg/1 g; SUNFLOWER OIL 64 mg/1 g

Drug Facts

Active ingredient

Zinc Oxide….20.0%

Purpose

Sunscreen

Keep Out of Reach of Children

If swallowed; get medical help or contact a Poison Control Center right away.

Uses

Helps prevent sunburn. If used as directed with other sun protection measures (See Directions), decreases the risk of skin cancer and early skin aging caused by the sun.

Warnings

For external use only. Do not use on damaged or broken skin. When using this product keep out of eyes. Rinse with water to remove. Stop use and ask a doctor if rash occurs.

Directions

Apply liberally 15 minutes before sun exposure. Reapply after 80 minutes of swimming or sweating. Immediately after towel drying. At least every 2 hours. Sun Protection Measures. Spending time in the sun increases your risk of skin cancer and early skin aging. To decrease this risk regularly use a sunscreen with Broad Spectrum SPF value of 15 or higher and other sun protection measures including: Limit time in the sun especially from 10 a.m. – 2 p.m. Wear long-sleeve shirts, pants, hats and sunglasses. Children under 6 months: Ask a doctor.

Inactive Ingredients

Aloe Extract, Behenyl Behenate, Shea Butter, Caprylic/Capric Triglyceride, Coconut Oil, Candelilla Wax, Sunflower Oil, Sunflower Wax, Polyhydroxystearic Acid, Castor Oil, Jojoba Oil, Squalane, Cocoa Butter, Tocopherol (Vitamin E).